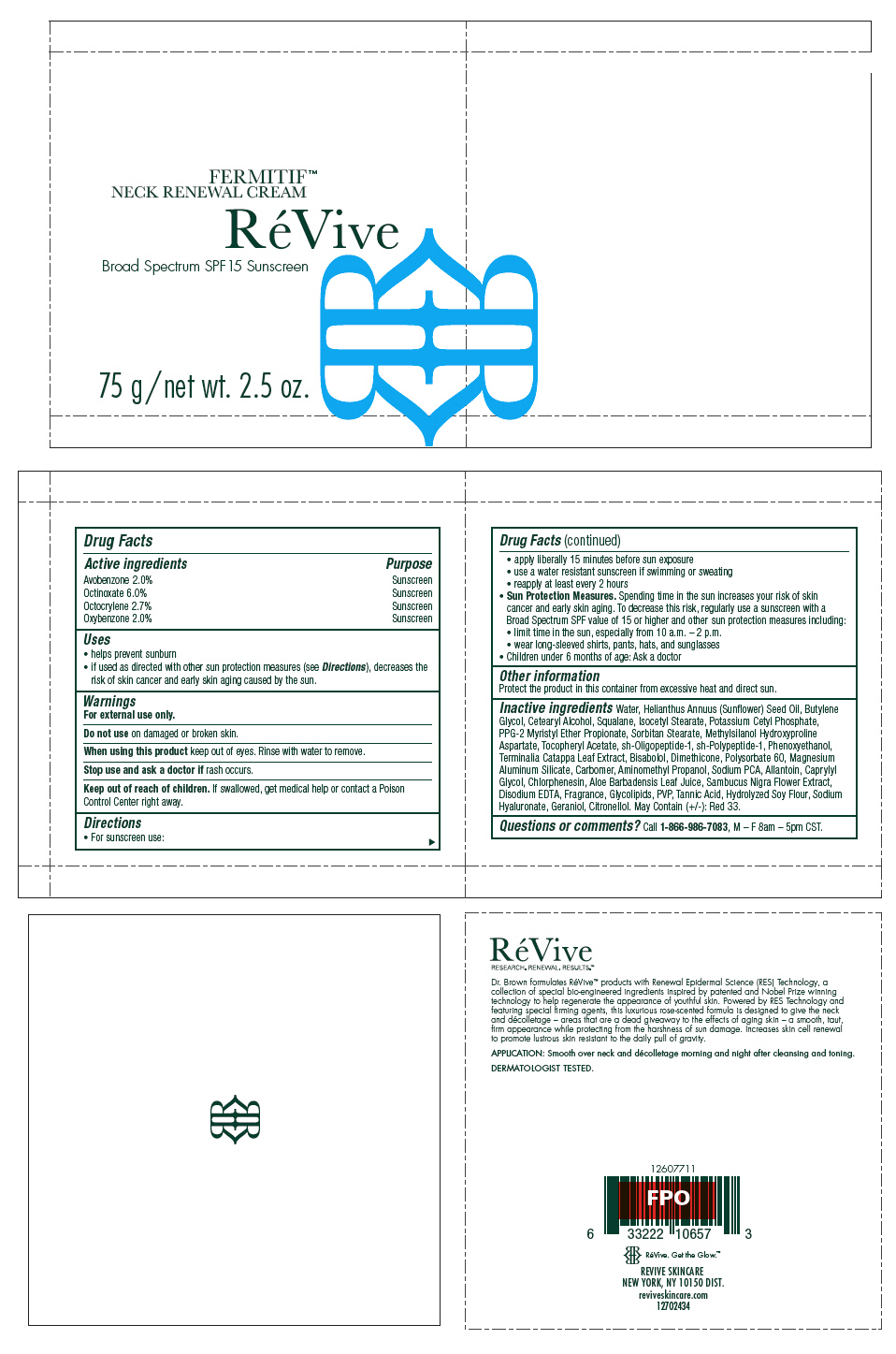 DRUG LABEL: ReVive Fermitif Neck Renewal 
NDC: 58411-416 | Form: CREAM
Manufacturer: RéVive Skincare
Category: otc | Type: HUMAN OTC DRUG LABEL
Date: 20180124

ACTIVE INGREDIENTS: AVOBENZONE 20 mg/1 g; OCTINOXATE 60 mg/1 g; OCTOCRYLENE 27 mg/1 g; OXYBENZONE 20 mg/1 g
INACTIVE INGREDIENTS: WATER; SUNFLOWER OIL; BUTYLENE GLYCOL; CETOSTEARYL ALCOHOL; SQUALANE; ISOCETYL STEARATE; POTASSIUM CETYL PHOSPHATE; PPG-2 MYRISTYL ETHER PROPIONATE; SORBITAN MONOSTEARATE; .ALPHA.-TOCOPHEROL ACETATE; NEPIDERMIN; BASIC FIBROBLAST GROWTH FACTOR (HUMAN); PHENOXYETHANOL; TERMINALIA CATAPPA LEAF; LEVOMENOL; DIMETHICONE; POLYSORBATE 60; MAGNESIUM ALUMINUM SILICATE; AMINOMETHYLPROPANOL; PYRROLIDONE CARBOXYLIC ACID; ALLANTOIN; CAPRYLYL GLYCOL; CHLORPHENESIN; ALOE VERA LEAF; SAMBUCUS NIGRA FLOWER; EDETATE DISODIUM ANHYDROUS; TANNIC ACID; HYALURONATE SODIUM; GERANIOL; D&C RED NO. 33

RéVive Fermitif™ Neck Renewal
Cream Broad Spectrum SPF 15 Sunscreen

Drug Facts

ACTIVE INGREDIENT

Active ingredients | Purpose
Avobenzone 2.0% | Sunscreen
Octinoxate 6.0% | Sunscreen
Octocrylene 2.7% | Sunscreen
Oxybenzone 2.0% | Sunscreen

Uses

- helps prevent sunburn
- if used as directed with other sun protection measures (see Directions), decreases the risk of skin cancer and early skin aging caused by the sun.

Warnings

For external use only.

Do not use on damaged or broken skin.

When using this product keep out of eyes. Rinse with water to remove.

Stop use and ask a doctor if rash occurs.

Keep out of reach of children. If swallowed, get medical help or contact a Poison Control Center right away.

Directions

- For sunscreen use:
  - apply liberally 15 minutes before sun exposure
  - use a water resistant sunscreen if swimming or sweating
  - reapply at least every 2 hours
- Sun Protection Measures. Spending time in the sun increases your risk of skin cancer and early skin aging. To decrease this risk, regularly use a sunscreen with a Broad Spectrum SPF value of 15 or higher and other sun protection measures including:
  - limit time in the sun, especially from 10 a.m. – 2 p.m.
  - wear long-sleeved shirts, pants, hats, and sunglasses
- Children under 6 months of age: Ask a doctor

Other information

Protect the product in this container from excessive heat and direct sun.

Inactive ingredients

Water, Helianthus Annuus (Sunflower) Seed Oil, Butylene Glycol, Cetearyl Alcohol, Squalane, Isocetyl Stearate, Potassium Cetyl Phosphate, PPG-2 Myristyl Ether Propionate, Sorbitan Stearate, Methylsilanol Hydroxyproline Aspartate, Tocopheryl Acetate, sh-Oligopeptide-1, sh-Polypeptide-1, Phenoxyethanol, Terminalia Catappa Leaf Extract, Bisabolol, Dimethicone, Polysorbate 60, Magnesium Aluminum Silicate, Carbomer, Aminomethyl Propanol, Sodium PCA, Allantoin, Caprylyl Glycol, Chlorphenesin, Aloe Barbadensis Leaf Juice, Sambucus Nigra Flower Extract, Disodium EDTA, Fragrance, Glycolipids, PVP, Tannic Acid, Hydrolyzed Soy Flour, Sodium Hyaluronate, Geraniol, Citronellol. May Contain (+/-): Red 33.

Questions or comments?

Call 1-866-986-7083, M – F 8am – 5pm CST.

PRINCIPAL DISPLAY PANEL - 75 g Jar Carton

FERMITIF™
NECK RENEWAL CREAM

RéVive

Broad Spectrum SPF15 Sunscreen

75 g/net wt. 2.5 oz.